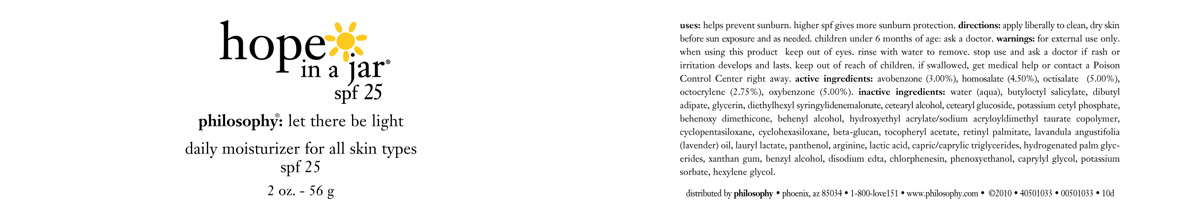 DRUG LABEL: Hope In A Jar SPF 25
NDC: 50184-6200 | Form: CREAM
Manufacturer: Philosophy, Inc.
Category: otc | Type: HUMAN OTC DRUG LABEL
Date: 20100525

ACTIVE INGREDIENTS: avobenzone 30 mg/1 g; homosalate 45 mg/1 g; octisalate 50 mg/1 g; octocrylene 27.5 mg/1 g; oxybenzone 50 mg/1 g

ACTIVE INGREDIENTS

ACTIVE INGREDIENT

AVOBENZONE (3.00%)

HOMOSALATE (4.50%)

OCTISALATE (5.00%)

OCTOCRYLENE (2.75%)

OXYBENZONE (5.00%)

INACTIVE INGREDIENTS:

water (aqua), butyloctyl salicylate, dibutyl adipate, glycerin, diethylhexyl syringylidenemalonate, cetearyl alcohol, cetearyl glucoside, potassium cetyl phosphate, behenoxy dimethicone, behenyl alcohol, hydroxyethyl acrylate/sodium acryloyldimethyl taurate copolymer, cyclopentasiloxane, cyclohexasiloxane, beta-glucan, tocopheryl acetate, retinyl palmitate, lavandula angustifolia (lavender) oil, lauryl lactate, panthenol, arginine, lactic acid, capric/caprylic triglycerides, hydrogenated palm glycerides, xanthan gum, benzyl alcohol, disodium edta, chlorphenesin, phenoxyethanol, caprylyl glycol, potassium sorbate, hexylene glycol.

STOP USE AND ASK DOCTOR IF RASH OR IRRITATION DEVELOPS AND LASTS.

WARNINGS

FOR EXTERNAL USE ONLY.

WHEN USING THIS PRODUCT KEEP OUT OF EYES, RINSE WITH WARM WATER TO REMOVE.

KEEP OUT OF REACH OF CHILDREN. IF SWALLOWED GET MEDICAL HELP OR CONTACT A POISON CONTROL CENTER RIGHT AWAY.